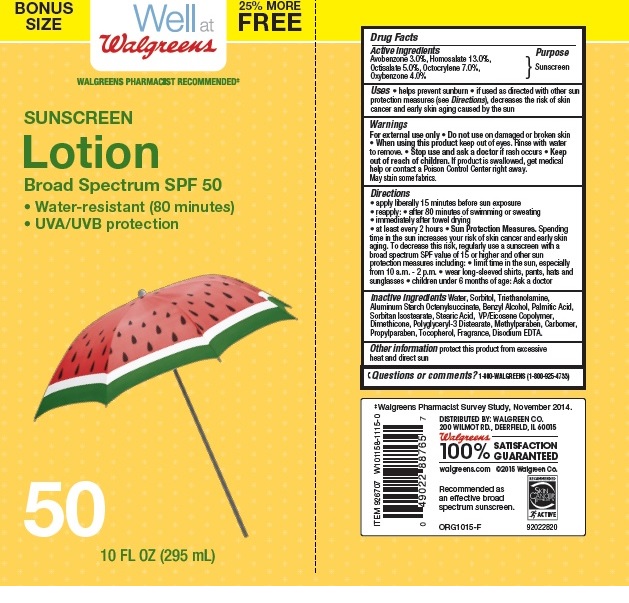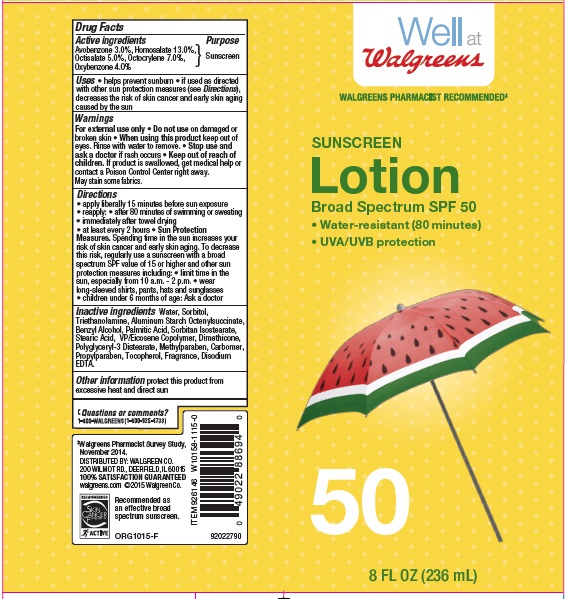 DRUG LABEL: Walgreens Sunscreen
NDC: 0363-4007 | Form: LOTION
Manufacturer: WALGREEN CO.
Category: otc | Type: HUMAN OTC DRUG LABEL
Date: 20161020

ACTIVE INGREDIENTS: AVOBENZONE 3 g/100 g; HOMOSALATE 13 g/100 g; OCTISALATE 5 g/100 g; OCTOCRYLENE 7 g/100 g; OXYBENZONE 4 g/100 g
INACTIVE INGREDIENTS: WATER; SORBITOL; STEARIC ACID; TROLAMINE; ALUMINUM STARCH OCTENYLSUCCINATE; BENZYL ALCOHOL; SORBITAN ISOSTEARATE; DIMETHICONE; METHYLPARABEN; TOCOPHEROL; EDETATE DISODIUM; PROPYLPARABEN

Drug Facts

Active ingredients

Avobenzone 3.0 %, Homosalate 13.0%, Octisalate 5.0%, Octocrylene 7.0%, Oxybenzone 4.0%

Purpose

Sunscreen

Uses

- helps prevent sunburn
- if used as directed with other sun protection measures (see Directions), decreases the risk of skin cancer and early skin aging caused by the sun.

Warnings

For external use only

Do not use

- on damaged or broken skin

When using this product

- keep out of eyes. Rinse with water to remove

stop use and ask a doctor

- if rash occurs

keep out of reach of children

If product is swallowed, get medical help or contact a Poison Control Center right away.

- May stain some fabrics

Directions

- apply liberally 15 minutes before sun exposure
- reapply: after 80 minutes of swimming or sweating
- immediately after towel drying
- at least every 2 hours
- Sun Protection measures. Spending time in the sun increases your risk of skin cancer and early skin aging. To decrease this risk, regularly use a sunscreen with a broad spectrum SPF value of 15 or higher and other sun protection measures including
- limit time in the sun, especially from 10 a.m. - 2 p.m.
- wear long-sleeved shirts, pants, hats and sunglasses
- children under 6 months of age:Ask a doctor

Inactive ingredients

Water, Sorbitol, Stearic Acid, Triethanolamine, Aluminum Starch Octenylsuccinate, Benzyl Alcohol, Sorbitan Isostearate, VP/Eicosene Copolymer, Dimethicone, Polyglyceryl-3 Distearate, Carbomer, Tocopherol, Disodium EDTA, Methylparaben, Propylparaben, Fragrance.

other information

protect this product from excessive heat and direct sun

Questions or Comments?

1-800-WALGREENS (1-800-925-4733)

Principal Display Panel

NDC: 0363-4007-19

Well at Walgreens

WALGREENS PHARMACIST RECOMMENDED

SUNSCREEN Lotion

Broad Spectrum SPF 50

- Water-resistant (80 minutes)
- UVA/UVB protection

50

8 FL OZ (236 mL)

NDC: 0363-4007-22

BONUS SIZE 25% MORE FREE

Well at Walgreens

WALGREENS PHARMACIST RECOMMENDED

SUNSCREEN Lotion

Broad Spectrum SPF 50

- Water-resistant (80 minutes)
- UVA/UVB protection

50

10 FL OZ (295 mL)